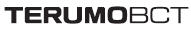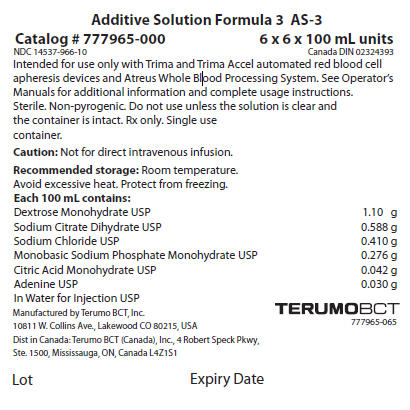 DRUG LABEL: AS 
NDC: 14537-966 | Form: INJECTION, SOLUTION
Manufacturer: Terumo BCT Ltd
Category: prescription | Type: HUMAN PRESCRIPTION DRUG LABEL
Date: 20250122

ACTIVE INGREDIENTS: Dextrose Monohydrate 1.1 g/100 mL; SODIUM CITRATE, UNSPECIFIED FORM 0.588 g/100 mL; Sodium Chloride 0.41 g/100 mL; Sodium Phosphate, Monobasic, Monohydrate 0.276 g/100 mL; Citric Acid Monohydrate 0.042 g/100 mL; Adenine 0.03 g/100 mL

Additive Solution Formula 3

Catalog # 777965-000
6 x 6 x 100 mL units

NDC 14537-966-10
Canada DIN 02324393

DESCRIPTION

Intended for use only with Trima and Trima Accel automated red blood cell apheresis devices and Atreus Whole Blood Processing System. See Operator's Manuals for additional information and complete usage instructions.

Sterile. Non-pyrogenic. Do not use unless the solution is clear and the container is intact. Rx only.

Single use container.

Caution: Not for direct intravenous infusion.

Recommended storage

Room temperature.

Avoid excessive heat. Protect from freezing.

HOW SUPPLIED

Each 100 mL contains:

Dextrose Monohydrate USP | 1.10 g
Sodium Citrate Dihydrate USP | 0.588 g
Sodium Chloride USP | 0.410 g
Monobasic Sodium Phosphate Monohydrate USP | 0.276 g
Citric Acid Monohydrate USP | 0.042 g
Adenine USP | 0.030 g
In Water for Injection USP

Manufactured by Terumo BCT, Inc.
10811 W. Collins Ave., Lakewood CO 80215, USA

Dist in Canada: Terumo BCT (Canada), Inc., 4 Robert Speck Pkwy,
Ste. 1500, Mississauga, ON, Canada L4Z1S1

777965-065

Lot
Expiry Date

PRINCIPAL DISPLAY PANEL - 100 mL Label

Additive Solution Formula 3 AS-3

Catalog # 777965-000
6 x 6 x 100 mL units

NDC 14537-966-10
Canada DIN 02324393

Intended for use only with Trima and Trima Accel automated red blood cell
apheresis devices and Atreus Whole Blood Processing System. See Operator's
Manuals for additional information and complete usage instructions.
Sterile. Non-pyrogenic. Do not use unless the solution is clear and
the container is intact. Rx only. Single use
container.

Caution: Not for direct intravenous infusion.

Recommended storage: Room temperature.
Avoid excessive heat. Protect from freezing.

Each 100 mL contains:

Dextrose Monohydrate USP | 1.10 g
Sodium Citrate Dihydrate USP | 0.588 g
Sodium Chloride USP | 0.410 g
Monobasic Sodium Phosphate Monohydrate USP | 0.276 g
Citric Acid Monohydrate USP | 0.042 g
Adenine USP | 0.030 g
In Water for Injection USP

Manufactured by Terumo BCT, Inc.
10811 W. Collins Ave., Lakewood CO 80215, USA
Dist in Canada: Terumo BCT (Canada), Inc., 4 Robert Speck Pkwy,
Ste. 1500, Mississauga, ON, Canada L4Z1S1

TERUMOBCT
777965-065

Lot
Expiry Date